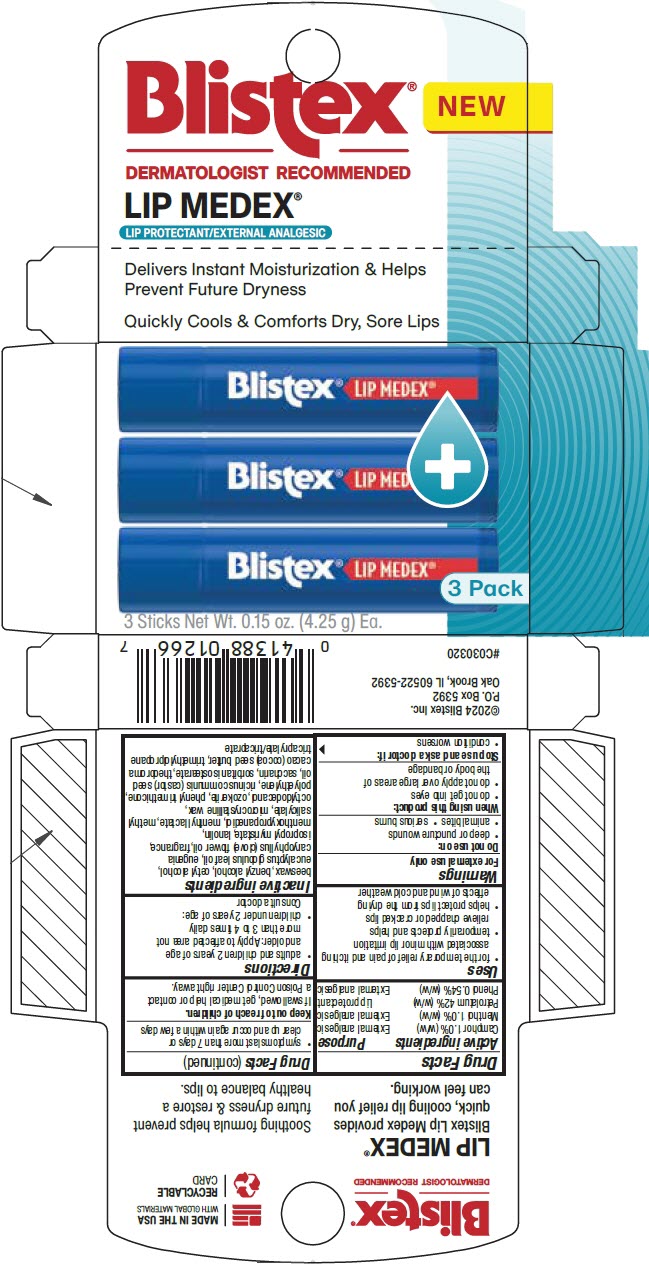 DRUG LABEL: Lip Medex Lip Balm
NDC: 10157-1194 | Form: STICK
Manufacturer: Blistex Inc.
Category: otc | Type: HUMAN OTC DRUG LABEL
Date: 20240701

ACTIVE INGREDIENTS: PETROLATUM 42 g/100 g; CAMPHOR (SYNTHETIC) 1 g/100 g; MENTHOL, UNSPECIFIED FORM 1 g/100 g; PHENOL 0.6 g/100 g
INACTIVE INGREDIENTS: CERESIN; MICROCRYSTALLINE WAX; LANOLIN; OCTYLDODECANOL; TRIMETHYLOLPROPANE TRICAPRYLATE/TRICAPRATE; YELLOW WAX; PHENYL TRIMETHICONE; HIGH DENSITY POLYETHYLENE; ISOPROPYL MYRISTATE; COCOA BUTTER; SORBITAN ISOSTEARATE; MENTHYL LACTATE, (-)-; BENZYL ALCOHOL; 3-((L-MENTHYL)OXY)PROPANE-1,2-DIOL; CETYL ALCOHOL; METHYL SALICYLATE; CASTOR OIL; SACCHARIN; EUCALYPTUS OIL; CLOVE OIL

Lip Medex® Lip Balm

Drug Facts

ACTIVE INGREDIENT

Active ingredients | Purpose
Camphor 1.0% (w/w) | External analgesic
Menthol 1.0% (w/w) | External analgesic
Petrolatum 42% (w/w) | Lip protectant
Phenol 0.54% (w/w) | External analgesic

Uses

- for the temporary relief of pain and itching associated with minor lip irritation
- temporarily protects and helps relieve chapped or cracked lips
- helps protect lips from the drying effects of wind and cold weather

Warnings

For external use only

Do not use on:

- deep or puncture wounds
- animal bites
- serious burns

When using this product:

- do not get into eyes
- do not apply over large areas of the body or bandage

Stop use and ask a doctor if:

- condition worsens
- symptoms last more than 7 days or clear up and occur again within a few days

Keep out of reach of children.

If swallowed, get medical help or contact a Poison Control Center right away.

Directions

- adults and children 2 years of age and older: Apply to affected area not more than 3 to 4 times daily
- children under 2 years of age: Consult a doctor

Inactive ingredients

beeswax, benzyl alcohol, cetyl alcohol, eucalyptus globulus leaf oil, eugenia caryophyllus (clove) flower oil, fragrance, isopropyl myristate, lanolin, menthoxypropanediol, menthyl lactate, methyl salicylate, microcrystalline wax, octyldodecanol, ozokerite, phenyl trimethicone, polyethylene, ricinus communis (castor) seed oil, saccharin, sorbitan isostearate, theobroma cacao (cocoa) seed butter, trimethylolpropane tricaprylate/tricaprate

PRINCIPAL DISPLAY PANEL - 4.25 g Stick Carton

Blistex®
NEW

DERMATOLOGIST RECOMMENDED

LIP MEDEX®

LIP PROTECTANT/EXTERNAL ANALGESIC

Delivers Instant Moisturization & Helps
Prevent Future Dryness

Quickly Cools & Comforts Dry, Sore Lips

3 Pack

3 Sticks Net Wt. 0.15 oz. (4.25 g) Ea.